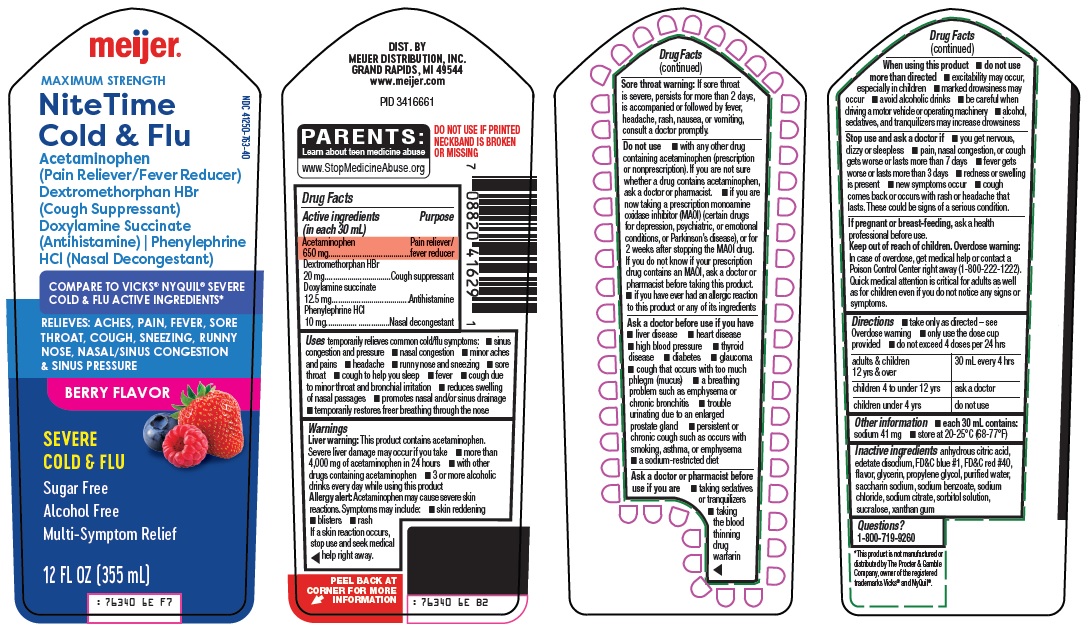 DRUG LABEL: Nitetime Cold and Flu
NDC: 41250-763 | Form: SOLUTION
Manufacturer: Meijer Distribution Inc
Category: otc | Type: HUMAN OTC DRUG LABEL
Date: 20251013

ACTIVE INGREDIENTS: ACETAMINOPHEN 650 mg/30 mL; DEXTROMETHORPHAN HYDROBROMIDE 20 mg/30 mL; DOXYLAMINE SUCCINATE 12.5 mg/30 mL; PHENYLEPHRINE HYDROCHLORIDE 10 mg/30 mL
INACTIVE INGREDIENTS: ANHYDROUS CITRIC ACID; EDETATE DISODIUM; FD&C BLUE NO. 1; FD&C RED NO. 40; GLYCERIN; PROPYLENE GLYCOL; WATER; SACCHARIN SODIUM; SODIUM BENZOATE; SODIUM CHLORIDE; SODIUM CITRATE, UNSPECIFIED FORM; SORBITOL SOLUTION; SUCRALOSE; XANTHAN GUM

Meijer Distribution, Inc. NiteTime Cold & Flu Drug Facts

Active ingredients (in each 30 mL)

Acetaminophen 650 mg

Dextromethorphan HBr 20 mg

Doxylamine succinate 12.5 mg

Phenylephrine HCl 10 mg

Purpose

Pain reliever/fever reducer

Cough suppressant

Antihistamine

Nasal decongestant

Uses

temporarily relieves common cold/flu symptoms:

- nasal congestion
- sinus congestion and pressure
- minor aches and pains
- headache
- fever
- sore throat
- runny nose and sneezing
- cough due to minor throat and bronchial irritation
- cough to help you sleep
- reduces swelling of nasal passages
- promotes nasal and/or sinus drainage
- temporarily restores freer breathing through the nose

Warnings

Liver warning: This product contains acetaminophen. Severe liver damage may occur if you take

- more than 4,000 mg of acetaminophen in 24 hours
- with other drugs containing acetaminophen
- 3 or more alcoholic drinks every day while using this product

Allergy alert: Acetaminophen may cause severe skin reactions. Symptoms may include:

- skin reddening
- blisters
- rash

If a skin reaction occurs, stop use and seek medical help right away.

Sore throat warning: If sore throat is severe, persists for more than 2 days, is accompanied or followed by fever, headache, rash, nausea, or vomiting, consult a doctor promptly.

Do not use

- with any other drug containing acetaminophen (prescription or nonprescription). If you are not sure whether a drug contains acetaminophen, ask a doctor or pharmacist.
- if you are now taking a prescription monoamine oxidase inhibitor (MAOI) (certain drugs for depression, psychiatric, or emotional conditions, or Parkinson’s disease), or for 2 weeks after stopping the MAOI drug. If you do not know if your prescription drug contains an MAOI, ask a doctor or pharmacist before taking this product.
- if you have ever had an allergic reaction to this product or any of its ingredients

Ask doctor before use if you have

- liver disease
- heart disease
- high blood pressure
- thyroid disease
- diabetes
- glaucoma
- cough that occurs with too much phlegm (mucus)
- a breathing problem such as emphysema or chronic bronchitis
- trouble urinating due to an enlarged prostate gland
- persistent or chronic cough such as occurs with smoking, asthma, or emphysema
- a sodium-restricted diet

Ask doctor or pharmacist before use if you are

- taking sedatives or tranquilizers
- taking the blood thinning drug warfarin

When using this product

- do not use more than directed
- excitability may occur, especially in children
- marked drowsiness may occur
- avoid alcoholic drinks
- be careful when driving a motor vehicle or operating machinery
- alcohol, sedatives, and tranquilizers may increase drowsiness

Stop use and ask a doctor if

- you get nervous, dizzy or sleepless
- pain, nasal congestion, or cough gets worse or lasts more than 7 days
- fever gets worse or lasts more than 3 days
- redness or swelling is present
- new symptoms occur
- cough comes back or occurs with rash or headache that lasts. These could be signs of a serious condition.

If pregnant or breast-feeding,

ask a health professional before use.

Keep out of reach of children.

Overdose warning: In case of overdose, get medical help or contact a Poison Control Center right away (1-800-222-1222). Quick medical attention is critical for adults as well as for children even if you do not notice any signs or symptoms.

Directions

- take only as directed – see Overdose warning
- only use the dose cup provided
- do not exceed 4 doses per 24 hrs

adults & children 12 yrs & over | 30 mL every 4 hrs
children 4 to under 12 yrs | ask a doctor
children under 4 yrs | do not use

Other information

- each 30 mL contains: sodium 41 mg
- store at 20-25°C (68-77°F)

Inactive ingredients

anhydrous citric acid, edetate disodium, FD&C blue #1, FD&C red #40, flavor, glycerin, propylene glycol, purified water, saccharin sodium, sodium benzoate, sodium chloride, sodium citrate, sorbitol solution, sucralose, xanthan gum

Questions?

1-800-719-9260

Package/Label Principal Display Panel

meijer®

MAXIMUM STRENGTH

NiteTime Cold & Flu

Acetaminophen (Pain Reliever/Fever Reducer)

Dextromethorphan HBr (Cough Suppressant)

Doxylamine Succinate (Antihistamine)

Phenylephrine HCl (Nasal Decongestant)

COMPARE TO VICKS® NYQUIL® SEVERE COLD & FLU ACTIVE INGREDIENTS

RELIEVES: ACHES, PAIN, FEVER, SORE THROAT, COUGH, SNEEZING, RUNNY NOSE, NASAL/SINUS CONGESTION & SINUS PRESSURE

BERRY FLAVOR

SEVERE COLD & FLU

Sugar Free

Alcohol Free

Multi-Symptom Relief

12 FL OZ (355 mL)